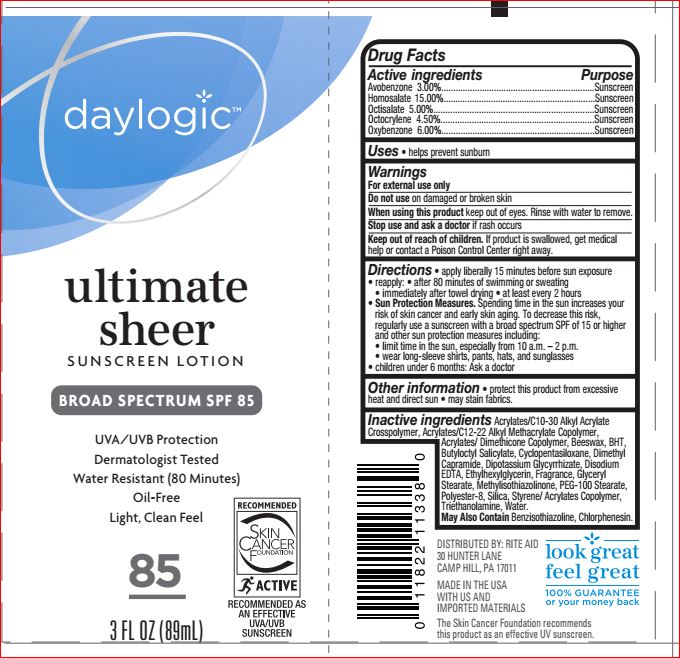 DRUG LABEL: Ultimate Sheer Sunscreen SPF 85
NDC: 11822-1111 | Form: LOTION
Manufacturer: Ride Aid
Category: otc | Type: HUMAN OTC DRUG LABEL
Date: 20171024

ACTIVE INGREDIENTS: Avobenzone 3.00 g/100 mL; Homosalate 15.00 g/100 mL; Octisalate 5.00 g/100 mL; Octocrylene 4.50 g/100 mL; Oxybenzone 6.00 g/100 mL
INACTIVE INGREDIENTS: CARBOMER INTERPOLYMER TYPE A (ALLYL SUCROSE CROSSLINKED); YELLOW WAX; BUTYLATED HYDROXYTOLUENE; Butyloctyl Salicylate; CYCLOMETHICONE 5; Dimethyl Capramide; GLYCYRRHIZINATE DIPOTASSIUM; EDETATE DISODIUM; Ethylhexylglycerin; GLYCERYL MONOSTEARATE; Methylisothiazolinone; PEG-100 Stearate; POLYESTER-8 (1400 MW, CYANODIPHENYLPROPENOYL CAPPED); SILICON DIOXIDE; STYRENE/ACRYLAMIDE COPOLYMER (MW 500000); TROLAMINE; Water

Active ingredients Purpose
Avobenzone 3.00%...............................................................Sunscreen
Homosalate 15.00%..............................................................Sunscreen
Octisalate 5.00%...................................................................Sunscreen
Octocrylene 4.50%................................................................Sunscreen
Oxybenzone 6.00%...............................................................Sunscreen

INDICATIONS AND USAGE

Uses • helps prevent sunburn

Warnings
For external use only
Do not use on damaged or broken skin
When using this product keep out of eyes. Rinse with water to remove.
Stop use and ask a doctor if rash occurs
Keep out of reach of children. If product is swallowed, get medical
help or contact a Poison Control Center right away.

DOSAGE AND ADMINISTRATION

Directions • apply liberally 15 minutes before sun exposure
• reapply: • after 80 minutes of swimming or sweating
• immediately after towel drying • at least every 2 hours
• Sun Protection Measures. Spending time in the sun increases your
risk of skin cancer and early skin aging. To decrease this risk,
regularly use a sunscreen with a broad spectrum SPF of 15 or higher
and other sun protection measures including:
• limit time in the sun, especially from 10 a.m. – 2 p.m.
• wear long-sleeve shirts, pants, hats, and sunglasses
• children under 6 months: Ask a doctor

Inactive ingredients Acrylates/C10-30 Alkyl Acrylate
Crosspolymer, Acrylates/C12-22 Alkyl Methacrylate Copolymer,
Acrylates/ Dimethicone Copolymer, Beeswax, BHT,
Butyloctyl Salicylate, Cyclopentasiloxane, Dimethyl
Capramide, Dipotassium Glycyrrhizate, Disodium
EDTA, Ethylhexylglycerin, Fragrance, Glyceryl
Stearate, Methylisothiazolinone, PEG-100 Stearate,
Polyester-8, Silica, Styrene/ Acrylates Copolymer,
Triethanolamine, Water.
May Also Contain Benzisothiazoline, Chlorphenesin